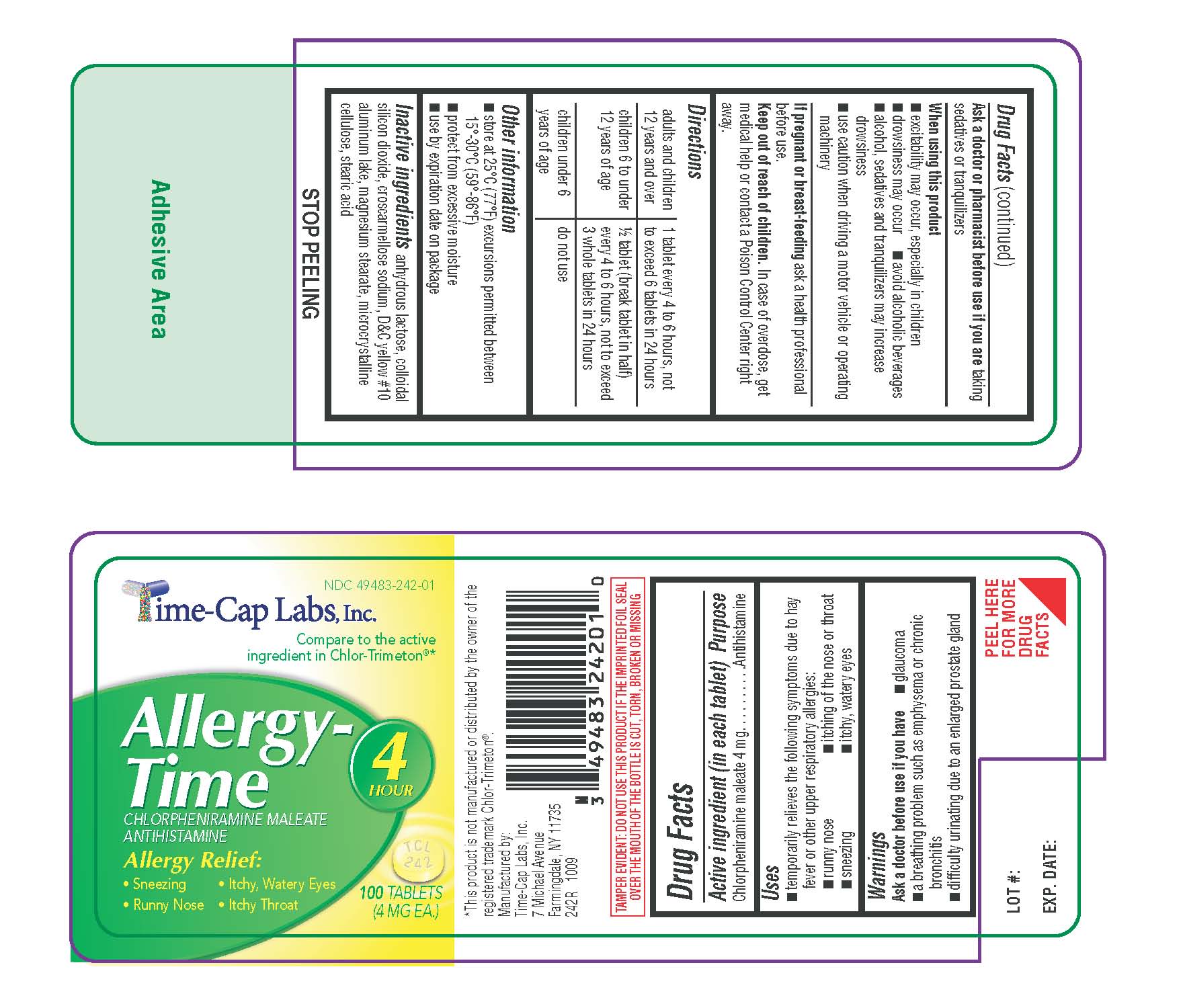 DRUG LABEL: Allergy Time
NDC: 49483-242 | Form: TABLET
Manufacturer: Time Cap Labs Inc
Category: otc | Type: HUMAN OTC DRUG LABEL
Date: 20181217

ACTIVE INGREDIENTS: CHLORPHENIRAMINE MALEATE 4 mg/1 1
INACTIVE INGREDIENTS: ANHYDROUS LACTOSE; SILICON DIOXIDE; CROSCARMELLOSE SODIUM; D&C YELLOW NO. 10; MAGNESIUM STEARATE; CELLULOSE, MICROCRYSTALLINE; STEARIC ACID

242R CHLOR MAL

Active ingredient (in each tablet) Chlorpheniramine maleate 4 mg

Purpose: Antihistamine

INDICATIONS AND USAGE

Uses: temporarily relieves the following symptoms due to hay fever or other upper respiratory allergies:

runny nose, sneezing, itching of the nose or throat, itch, watery eyes

Warnings

Ask a doctor before use if you have:

glaucoma; a breathing problem such as emphysema or chronic bronchitis; difficulty urinating due to an enlarged prostate gland

Ask a doctor or pharmacist before use if you are taking sedatives or tranquilizers.

When using this product:

excitability may occur, especially in children; drowsiness may occur; avoid alcoholic beverages; alcohol, sedatives and tranquilizers may increase drowsiness; use caution when driving a motor vehicle operating machinery

PREGNANCY OR BREAST FEEDING

If pregnant or breast-feeding ask a health professional before use.

Directions

Adults and children 12 years and over - 1 tablet every 4 to 6 hours, not to exceed 6 tablets in 24 hours

Children 6 to under 12 years of age - 1/2 tablet (break tablet in half) every 4 to 6 hours, not to exceed 3 whole tablets in 24 hours

Children under 6 years of age - do not use

KEEP OUT OF REACH OF CHILDREN

Keep out of the reach of children. In case of overdose, get medical help or contact a Poison Control Center right away.

INACTIVE INGREDIENT

anhydrous lactose, colloidal silicon dioxide, croscarmellose sodium, D-C yellow #10 aluminum lake, magnesium stearate, microcrystalline cellulose, stearic acid.